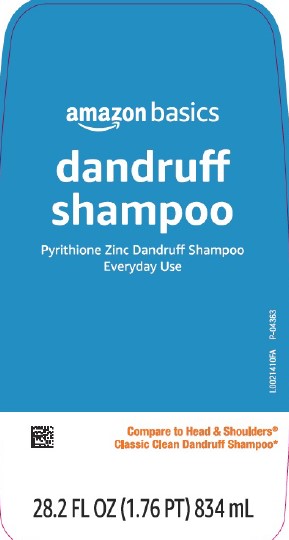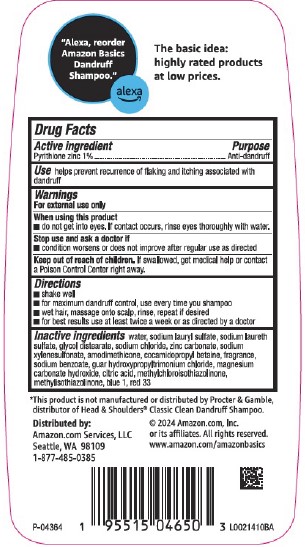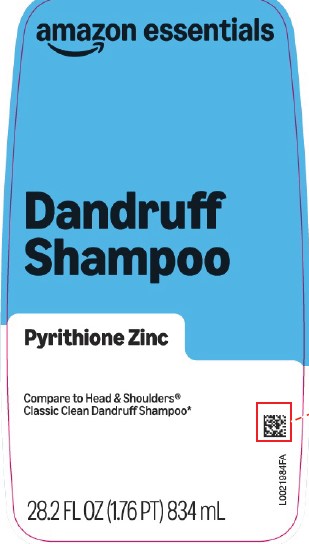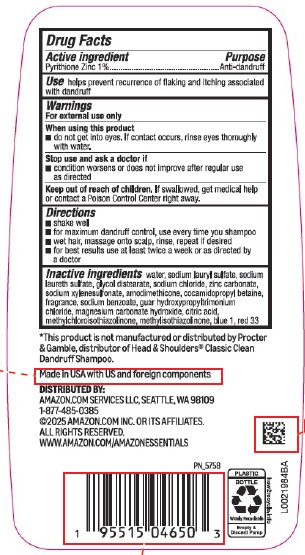 DRUG LABEL: Everyday Clean Dandruff
NDC: 72288-153 | Form: SHAMPOO
Manufacturer: Amazon.Com Services LLC
Category: otc | Type: HUMAN OTC DRUG LABEL
Date: 20260203

ACTIVE INGREDIENTS: PYRITHIONE ZINC 1 mg/1 mL
INACTIVE INGREDIENTS: WATER; SODIUM LAURYL SULFATE; SODIUM LAURETH SULFATE; GLYCOL DISTEARATE; SODIUM CHLORIDE; ZINC CARBONATE; SODIUM XYLENESULFONATE; AMODIMETHICONE (1300 CST); COCAMIDOPROPYL BETAINE; SODIUM BENZOATE; GUAR HYDROXYPROPYLTRIMONIUM CHLORIDE (1.7 SUBSTITUENTS PER SACCHARIDE); MAGNESIUM CARBONATE HYDROXIDE; CITRIC ACID MONOHYDRATE; METHYLCHLOROISOTHIAZOLINONE; METHYLISOTHIAZOLINONE; FD&C BLUE NO. 1; D&C RED NO. 33

Essentials_Basics 153.008/153AZ rev1 - BD
Everyday Clean Dandruff Shampoo

Active Ingredient

Pyrithione zinc 1%

Purpose

Anti-dandruff

Use

helps prevent recurrence of flaking and itching associated with dandruff

Warnings

For external use only

When using this product

- do not get into eyes. If contact occurs, rinse eyes thoroughly with water.

Stop use and ask a doctor if

- condition worsens or does not improve after regular use as directed

Keep out of reach of children.

If swallowed, get medical help or contact a Poison Control center right away.

Directions

- shake well
- for maximum dandruff control, use every time you shampoo
- wet hair, massage onto scalp, rinse, repeat if desired
- for best results use at least twice a week or as directed by a doctor

Inactive ingredients

water, sodium lauryl sulfate, sodium laureth sulfate, glycol distearate, sodium chloride, zinc carbonate, sodium xylenesulfonate, amodimethicone, cocamidopropyl betaine, fragrance, sodium benzoate, guar hydroxypropyltrimonium chloride, magnesium carbonate hydroxide, citric acid, methylchloroisothiazolinone, methylisothiazolinone, blue 1, red 33

Disclaimer

*This product is not manufactured or distributed by Procter & Gamble, distributor of Head & Shoulders® Classic Clean Dandruff Shampoo.

ADVERSE REACTIONS

Made in USA with US and foreign components.

DISTRIBUTED BY:

Amazon.com, Services, LLC, Seattle, WA 98109

1-877-485-0385

©2025 Amazon.com, Inc. or its affiliates.

All rights reserved.

www.amazon.com/amazonessentials

PLASTIC BOTTLE

Widely Recyclable

Empty & Discard Pump

how2recycle.info

Principal Display Panel

amazon essentials

Dandruff Shampoo

Pyrithione Zinc

Compare to Head & Shoulders®Classic Clean Dandruff Shampoo*

28.2 FL OZ (1.76 PT) 834 mL

Principal Display Panel

amazon basics

dandruff shampoo

Pyrithione Zinc Dandruff Shampoo

Everyday Use

28.2 FL OZ (1.76 PT) 834 mL

Compare to Head & Shoulders ®

Classic Clean Dandruff Shampoo*